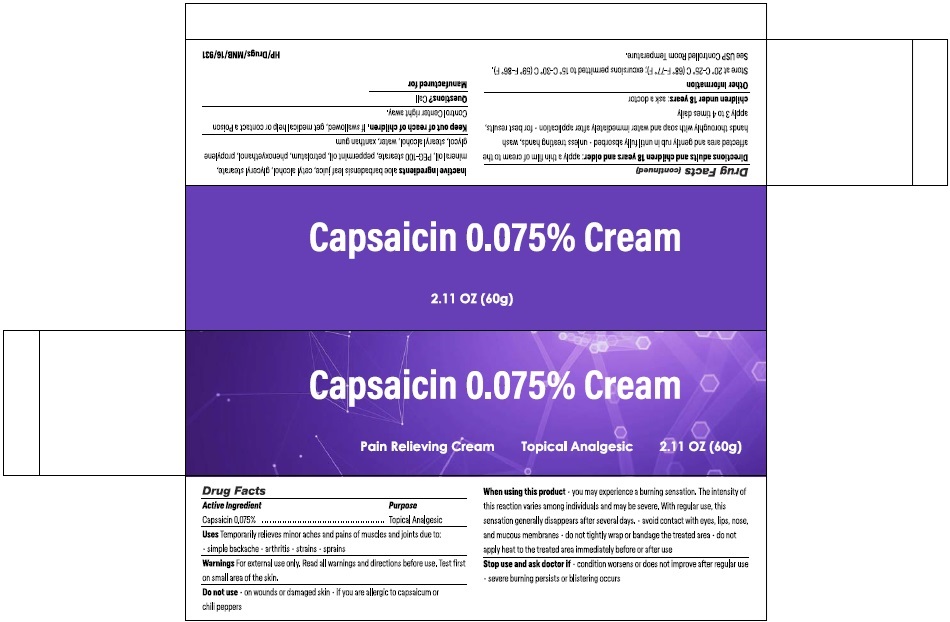 DRUG LABEL: Capsaicin Cream 0.075%
NDC: 73492-271 | Form: CREAM
Manufacturer: ALAINA HEALTHCARE PRIVATE LIMITED
Category: otc | Type: HUMAN OTC DRUG LABEL
Date: 20251209

ACTIVE INGREDIENTS: CAPSAICIN 0.075 g/100 g
INACTIVE INGREDIENTS: ALOE VERA LEAF JUICE; CETYL ALCOHOL; GLYCERYL MONOSTEARATE; MINERAL OIL; PEG-100 MONOSTEARATE; PEPPERMINT OIL; PETROLATUM; PHENOXYETHANOL; PROPYLENE GLYCOL; STEARYL ALCOHOL; WATER; XANTHAN GUM

Capsaicin 0.075% Cream

Drug facts Active Ingredient Purpose

Capsaicin 0.075%.............................................Topical Analgesic

Uses

Temporarily relieves minor aches and pains of muscles and joints due to:

- simple backache
- arthritis
- strains
- sprains

Warnings

For external use only. Read all warnings and directions before use. Test first on small area of the skin.

Do not use

- on wounds or damaged skin
- if you are allergic to capsaicum or chili peppers

When using this product

- you may experience a burning sensation. The intensity of this reaction varies among individuals and may be severe. With regular use, this sensation generally disappears after several days.
- avoid contact with eyes, lips, nose and mucous membranes
- do not tightly wrap or bandage the treated area
- do not apply heat to the treated area immediately before or after use

Stop use and ask doctor if

- condition worsens or does not improve after regular use
- severe burning persists or blistering occurs

DOSAGE AND ADMINISTRATION

Directions adults and children 18 years and older:

- apply a thin film of cream to the affected area and gently rub in until fully absorbed
- unless treating hands, wash hands thoroughly with soap and water immediately after application
- for best results, apply 3 to 4 times daily.

children under 18 years:ask a doctor

Other information

Store at 20° C-25° C (68° F-77° F); excursions permitted to 15° C-30° C (59° F-86° F). See USP Controlled Room Temperature.

Inactive Ingredients

aloe barbadensis leaf juice, cetyl alcohol, glyceryl stearate, mineral oil, PEG-100 stearate, peppermint oil, petrolatum, phenoxyethanol, propylene glycol, stearyl alcohol, water, xanthan gum

Keep out of reach of children.If swallowed, get medical help or contact a Poison Control Center right away.

Questions?Call

PRINCIPAL DISPLAY PANEL

Capsaicin 0.075% Cream
Pain Relieving Cream
Topical Analgesic
2.11 oz (60g)